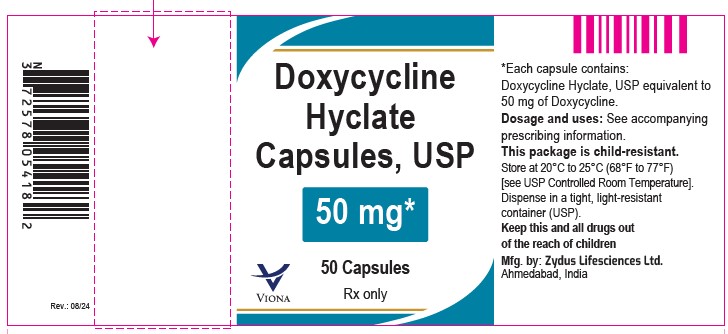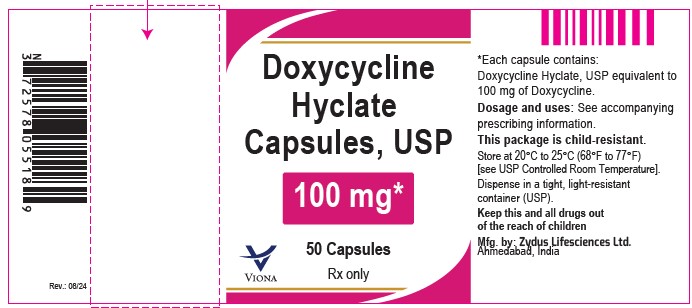 DRUG LABEL: Doxycycline hyclate
NDC: 70771-1358 | Form: CAPSULE
Manufacturer: Zydus Lifesciences Limited
Category: prescription | Type: HUMAN PRESCRIPTION DRUG LABEL
Date: 20240816

ACTIVE INGREDIENTS: DOXYCYCLINE HYCLATE 50 mg/1 1
INACTIVE INGREDIENTS: ALCOHOL; AMMONIA; ANHYDROUS LACTOSE; BUTYL ALCOHOL; CELLULOSE, MICROCRYSTALLINE; CROSCARMELLOSE SODIUM; D&C RED NO. 28; FD&C BLUE NO. 1; FERROSOFERRIC OXIDE; GELATIN; ISOPROPYL ALCOHOL; MAGNESIUM STEARATE; POTASSIUM HYDROXIDE; PROPYLENE GLYCOL; SHELLAC; SODIUM LAURYL SULFATE; TITANIUM DIOXIDE

Doxycycline hyclate capsules

PACKAGE LABEL.PRINCIPAL DISPLAY PANEL

NDC 70771-1358-7

Doxycycline hyclate capsules, 50 mg

Rx only

50 capsules

NDC 70771-1359-7

Doxycycline hyclate capsules, 100 mg

Rx only

50 capsules